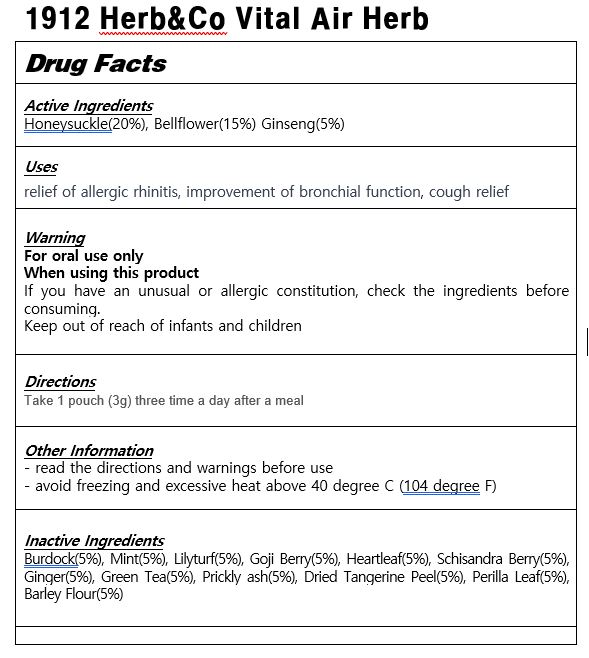 DRUG LABEL: 1912 Herb Co Vital Air Herb
NDC: 83933-0001 | Form: POWDER
Manufacturer: Agricultural Corporation YUBIMUHUAN CO Ltd
Category: otc | Type: HUMAN OTC DRUG LABEL
Date: 20240102

ACTIVE INGREDIENTS: LONICERA CAPRIFOLIUM FLOWER 20 g/100 g; PLATYCODON GRANDIFLORUS WHOLE 15 g/100 g; PANAX GINSENG ROOT OIL 5 g/100 g
INACTIVE INGREDIENTS: MINT

Drug Facts

ACTIVE INGREDIENT

Honeysuckle(20%), Bellflower(15%) Ginseng(5%)

INACTIVE INGREDIENT

Burdock(5%), Mint(5%), Lilyturf(5%), Goji Berry(5%), Heartleaf(5%), Schisandra Berry(5%), Ginger(5%), Green Tea(5%), Prickly ash(5%), Dried Tangerine Peel(5%), Perilla Leaf(5%), Barley Flour(5%)

PURPOSE

relief of allergic rhinitis, improvement of bronchial function, cough relief

keep out of reach of the children

INDICATIONS AND USAGE

Take 1 pouch (3g) three time a day after a meal

WARNINGS

If you have an unusual or allergic constitution, check the ingredients before consuming.

DOSAGE AND ADMINISTRATION

for oral use only